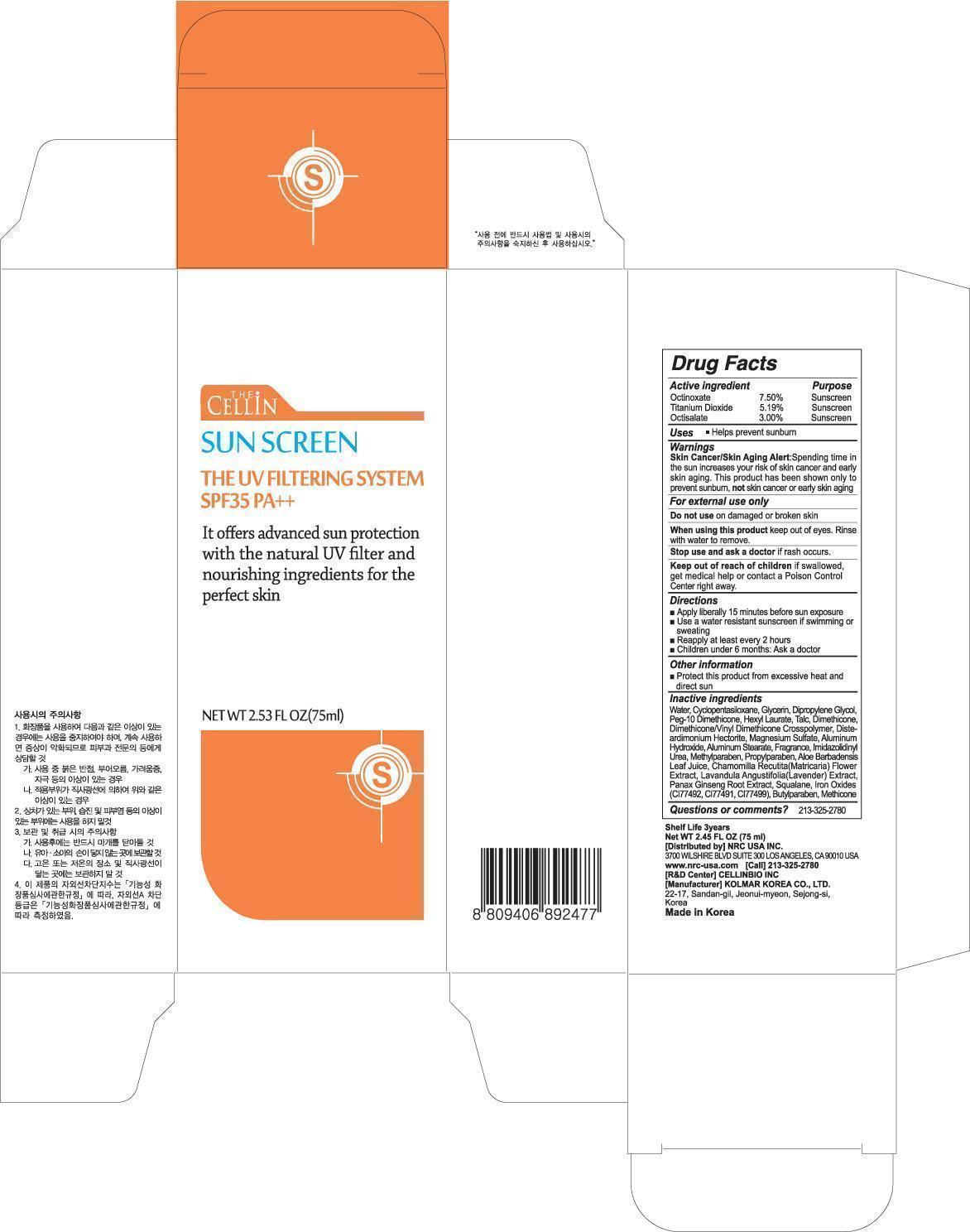 DRUG LABEL: THE CELLIN SUN SCREEN
NDC: 76173-1101 | Form: CREAM
Manufacturer: Cellinbio Co Ltd
Category: otc | Type: HUMAN OTC DRUG LABEL
Date: 20140926

ACTIVE INGREDIENTS: Octinoxate 5.62 mg/75 mL; Titanium Dioxide 3.89 mg/75 mL; Octisalate 2.25 mg/75 mL
INACTIVE INGREDIENTS: Water

ACTIVE INGREDIENT

Active ingredient: Octinoxate 7.50%, Titanium Dioxide 5.19%, Octisalate 3.00%

INACTIVE INGREDIENT

Inactive ingredients:
Water, Cyclopentasiloxane, Glycerin, Dipropylene Glycol, Peg-10 Dimethicone, Hexyl Laurate, Talc, Dimethicone, Dimethicone/Vinyl Dimethicone Crosspolymer, Diste-ardimonium Hectorite, Magnesium Sulfate, Aluminum Hydroxide, Aluminum Stearate, Fragrance, lmidazolidinyl Urea, Methylparaben, Propylparaben, Aloe Barbadensis Leaf Juice, Chamomilla Recutita(Matricaria) Flower Extract, Lavandula Angustifolia(Lavender) Extract, Panax Ginseng Root Extract, Squalane, Iron Oxides(CI77492, CI77491, CI77499), Butylparaben, Methicone

PURPOSE

Purpose: Sunscreen

WARNINGS

Skin Cancer/Skin Aging Alert: Spending time in the sun increases your risk of skin cancer and early skin aging. This product has been shown only to prevent sunburn, not skin cancer or early skin aging.
For external use only
Do not use on damaged or broken skin
When using this product keep out of eyes. Rinse with water to remove.
Stop use and ask a doctor if rash occurs

Keep out of reach of children if swallowed, get medical help or contact a Poison Control Center right away.

DESCRIPTION

Uses: Helps prevent sunburn

Directions:
- Apply liberally 15 minutes before sun exposure
- Use a water resistant sunscreen if swimming or sweating
- Reapply at least every 2 hours
- Children under 6 months : Ask a doctor

Other information:
Protect this product from excessive heat and direct sun

Questions or comments: 213-325-2780

Shelf Life 3years